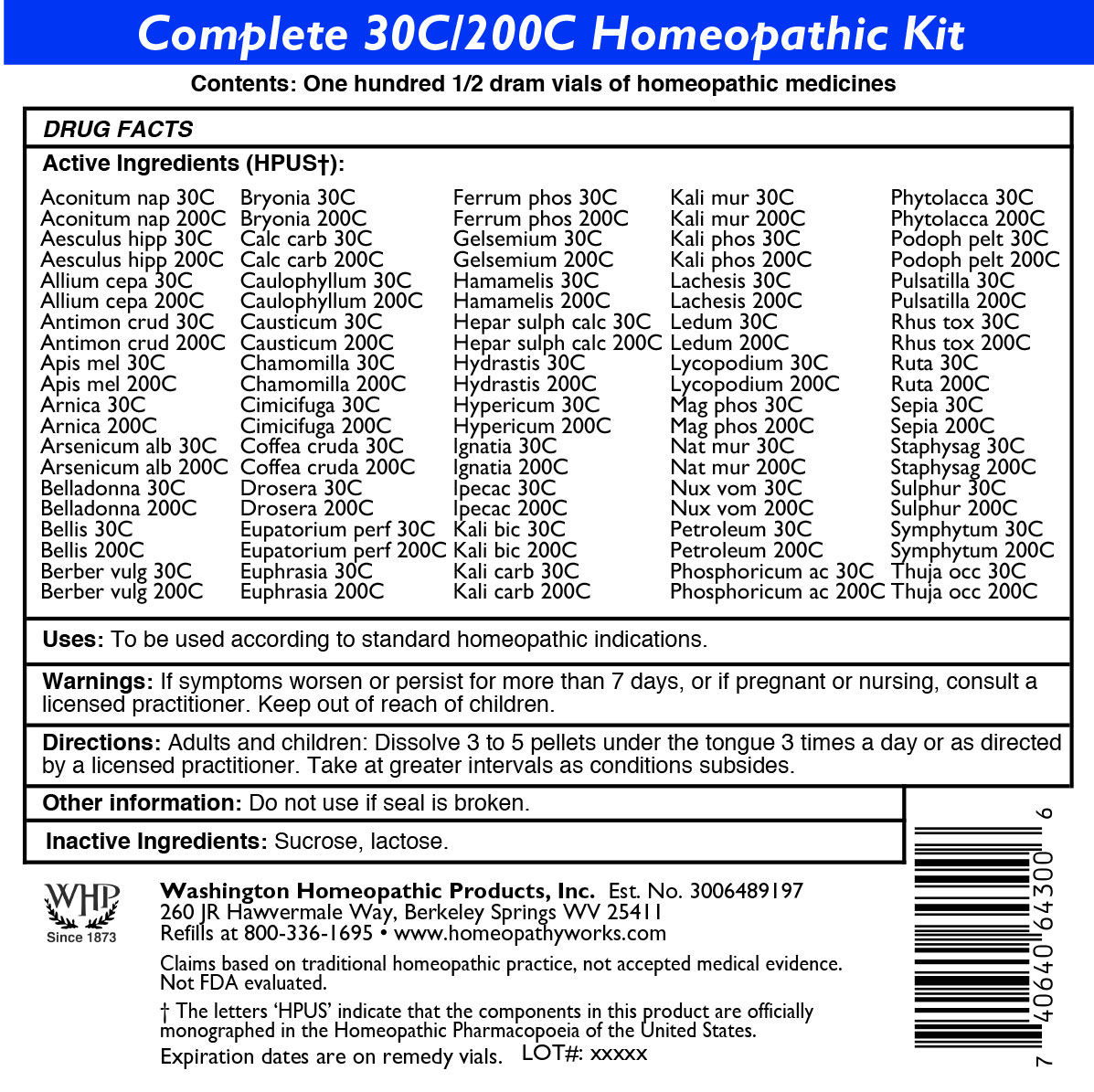 DRUG LABEL: Complete 30C/200C Homeopathic Kit
NDC: 71919-824 | Form: KIT | Route: ORAL
Manufacturer: Washington Homeopathic Products
Category: homeopathic | Type: HUMAN OTC DRUG LABEL
Date: 20260212

ACTIVE INGREDIENTS: ACONITUM NAPELLUS 30 [hp_C]/1 1; ACONITUM NAPELLUS 200 [hp_C]/1 1; HORSE CHESTNUT 30 [hp_C]/1 1; HORSE CHESTNUT 200 [hp_C]/1 1; ONION 200 [hp_C]/1 1; ONION 30 [hp_C]/1 1; ANTIMONY TRISULFIDE 30 [hp_C]/1 1; ANTIMONY TRISULFIDE 200 [hp_C]/1 1; APIS MELLIFERA 200 [hp_C]/1 1; APIS MELLIFERA 30 [hp_C]/1 1; ARNICA MONTANA 200 [hp_C]/1 1; ARNICA MONTANA 30 [hp_C]/1 1; ARSENIC TRIOXIDE 200 [hp_C]/1 1; ARSENIC TRIOXIDE 30 [hp_C]/1 1; ATROPA BELLADONNA 200 [hp_C]/1 1; ATROPA BELLADONNA 30 [hp_C]/1 1; BELLIS PERENNIS 30 [hp_C]/1 1; BELLIS PERENNIS 200 [hp_C]/1 1; BERBERIS VULGARIS ROOT BARK 30 [hp_C]/1 1; BERBERIS VULGARIS ROOT BARK 200 [hp_C]/1 1; BRYONIA ALBA ROOT 200 [hp_C]/1 1; BRYONIA ALBA ROOT 30 [hp_C]/1 1; OYSTER SHELL CALCIUM CARBONATE, CRUDE 200 [hp_C]/1 1; OYSTER SHELL CALCIUM CARBONATE, CRUDE 30 [hp_C]/1 1; CAULOPHYLLUM THALICTROIDES ROOT 200 [hp_C]/1 1; CAULOPHYLLUM THALICTROIDES ROOT 30 [hp_C]/1 1; CAUSTICUM 200 [hp_C]/1 1; CAUSTICUM 30 [hp_C]/1 1; MATRICARIA RECUTITA 200 [hp_C]/1 1; MATRICARIA RECUTITA 30 [hp_C]/1 1; BLACK COHOSH 30 [hp_C]/1 1; BLACK COHOSH 200 [hp_C]/1 1; ARABICA COFFEE BEAN 200 [hp_C]/1 1; ARABICA COFFEE BEAN 30 [hp_C]/1 1; DROSERA ROTUNDIFOLIA FLOWERING TOP 30 [hp_C]/1 1; DROSERA ROTUNDIFOLIA FLOWERING TOP 200 [hp_C]/1 1; EUPATORIUM PERFOLIATUM FLOWERING TOP 30 [hp_C]/1 1; EUPATORIUM PERFOLIATUM FLOWERING TOP 200 [hp_C]/1 1; EUPHRASIA STRICTA 200 [hp_C]/1 1; EUPHRASIA STRICTA 30 [hp_C]/1 1; FERROSOFERRIC PHOSPHATE 200 [hp_C]/1 1; FERROSOFERRIC PHOSPHATE 30 [hp_C]/1 1; GELSEMIUM SEMPERVIRENS ROOT 200 [hp_C]/1 1; GELSEMIUM SEMPERVIRENS ROOT 30 [hp_C]/1 1; HAMAMELIS VIRGINIANA ROOT BARK/STEM BARK 30 [hp_C]/1 1; HAMAMELIS VIRGINIANA ROOT BARK/STEM BARK 200 [hp_C]/1 1; CALCIUM SULFIDE 200 [hp_C]/1 1; CALCIUM SULFIDE 30 [hp_C]/1 1; GOLDENSEAL 200 [hp_C]/1 1; GOLDENSEAL 30 [hp_C]/1 1; HYPERICUM PERFORATUM 200 [hp_C]/1 1; HYPERICUM PERFORATUM 30 [hp_C]/1 1; STRYCHNOS IGNATII SEED 200 [hp_C]/1 1; STRYCHNOS IGNATII SEED 30 [hp_C]/1 1; IPECAC 200 [hp_C]/1 1; IPECAC 30 [hp_C]/1 1; POTASSIUM DICHROMATE 200 [hp_C]/1 1; POTASSIUM DICHROMATE 30 [hp_C]/1 1; POTASSIUM CARBONATE 30 [hp_C]/1 1; POTASSIUM CARBONATE 200 [hp_C]/1 1; POTASSIUM CHLORIDE 30 [hp_C]/1 1; POTASSIUM CHLORIDE 200 [hp_C]/1 1; POTASSIUM PHOSPHATE, DIBASIC 30 [hp_C]/1 1; LACHESIS MUTA VENOM 200 [hp_C]/1 1; LACHESIS MUTA VENOM 30 [hp_C]/1 1; LEDUM PALUSTRE TWIG 200 [hp_C]/1 1; LEDUM PALUSTRE TWIG 30 [hp_C]/1 1; LYCOPODIUM CLAVATUM SPORE 200 [hp_C]/1 1; LYCOPODIUM CLAVATUM SPORE 30 [hp_C]/1 1; MAGNESIUM PHOSPHATE, DIBASIC TRIHYDRATE 200 [hp_C]/1 1; MAGNESIUM PHOSPHATE, DIBASIC TRIHYDRATE 30 [hp_C]/1 1; SODIUM CHLORIDE 200 [hp_C]/1 1; SODIUM CHLORIDE 30 [hp_C]/1 1; STRYCHNOS NUX-VOMICA SEED 200 [hp_C]/1 1; STRYCHNOS NUX-VOMICA SEED 30 [hp_C]/1 1; KEROSENE 30 [hp_C]/1 1; KEROSENE 200 [hp_C]/1 1; PHOSPHORIC ACID 30 [hp_C]/1 1; PHOSPHORIC ACID 200 [hp_C]/1 1; PHYTOLACCA AMERICANA ROOT 200 [hp_C]/1 1; PHYTOLACCA AMERICANA ROOT 30 [hp_C]/1 1; PODOPHYLLUM 30 [hp_C]/1 1; PODOPHYLLUM 200 [hp_C]/1 1; PULSATILLA VULGARIS 200 [hp_C]/1 1; PULSATILLA VULGARIS 30 [hp_C]/1 1; TOXICODENDRON RADICANS LEAF 200 [hp_C]/1 1; TOXICODENDRON RADICANS LEAF 30 [hp_C]/1 1; RUTA GRAVEOLENS FLOWERING TOP 200 [hp_C]/1 1; RUTA GRAVEOLENS FLOWERING TOP 30 [hp_C]/1 1; SEPIA OFFICINALIS JUICE 200 [hp_C]/1 1; SEPIA OFFICINALIS JUICE 30 [hp_C]/1 1; DELPHINIUM STAPHISAGRIA SEED 200 [hp_C]/1 1; DELPHINIUM STAPHISAGRIA SEED 30 [hp_C]/1 1; SULFUR 200 [hp_C]/1 1; SULFUR 30 [hp_C]/1 1; COMFREY ROOT 200 [hp_C]/1 1; COMFREY ROOT 30 [hp_C]/1 1; THUJA OCCIDENTALIS LEAFY TWIG 200 [hp_C]/1 1; THUJA OCCIDENTALIS LEAFY TWIG 30 [hp_C]/1 1; POTASSIUM PHOSPHATE, DIBASIC 200 [hp_C]/1 1
INACTIVE INGREDIENTS: LACTOSE, UNSPECIFIED FORM; SUCROSE; LACTOSE, UNSPECIFIED FORM; SUCROSE; LACTOSE, UNSPECIFIED FORM; SUCROSE; LACTOSE, UNSPECIFIED FORM; SUCROSE; SUCROSE; LACTOSE, UNSPECIFIED FORM; LACTOSE, UNSPECIFIED FORM; SUCROSE; SUCROSE; LACTOSE, UNSPECIFIED FORM; SUCROSE; LACTOSE, UNSPECIFIED FORM; SUCROSE; LACTOSE, UNSPECIFIED FORM; LACTOSE, UNSPECIFIED FORM; SUCROSE; SUCROSE; LACTOSE, UNSPECIFIED FORM; SUCROSE; LACTOSE, UNSPECIFIED FORM; SUCROSE; LACTOSE, UNSPECIFIED FORM; SUCROSE; LACTOSE, UNSPECIFIED FORM; SUCROSE; LACTOSE, UNSPECIFIED FORM; SUCROSE; LACTOSE, UNSPECIFIED FORM; LACTOSE, UNSPECIFIED FORM; SUCROSE; LACTOSE, UNSPECIFIED FORM; SUCROSE; SUCROSE; LACTOSE, UNSPECIFIED FORM; LACTOSE, UNSPECIFIED FORM; SUCROSE; LACTOSE, UNSPECIFIED FORM; SUCROSE; LACTOSE, UNSPECIFIED FORM; SUCROSE; SUCROSE; LACTOSE, UNSPECIFIED FORM; SUCROSE; LACTOSE, UNSPECIFIED FORM; LACTOSE, UNSPECIFIED FORM; SUCROSE; SUCROSE; LACTOSE, UNSPECIFIED FORM; LACTOSE, UNSPECIFIED FORM; SUCROSE; SUCROSE; LACTOSE, UNSPECIFIED FORM; SUCROSE; LACTOSE, UNSPECIFIED FORM; LACTOSE, UNSPECIFIED FORM; SUCROSE; LACTOSE, UNSPECIFIED FORM; SUCROSE; LACTOSE, UNSPECIFIED FORM; SUCROSE; SUCROSE; LACTOSE, UNSPECIFIED FORM; LACTOSE, UNSPECIFIED FORM; SUCROSE; LACTOSE, UNSPECIFIED FORM; SUCROSE; SUCROSE; LACTOSE, UNSPECIFIED FORM; SUCROSE; LACTOSE, UNSPECIFIED FORM; LACTOSE, UNSPECIFIED FORM; SUCROSE; LACTOSE, UNSPECIFIED FORM; SUCROSE; SUCROSE; LACTOSE, UNSPECIFIED FORM; LACTOSE, UNSPECIFIED FORM; SUCROSE; LACTOSE, UNSPECIFIED FORM; SUCROSE; SUCROSE; LACTOSE, UNSPECIFIED FORM; LACTOSE, UNSPECIFIED FORM; SUCROSE; SUCROSE; LACTOSE, UNSPECIFIED FORM; SUCROSE; LACTOSE, UNSPECIFIED FORM; LACTOSE, UNSPECIFIED FORM; SUCROSE; SUCROSE; LACTOSE, UNSPECIFIED FORM; LACTOSE, UNSPECIFIED FORM; SUCROSE; LACTOSE, UNSPECIFIED FORM; SUCROSE; LACTOSE, UNSPECIFIED FORM; SUCROSE; SUCROSE; LACTOSE, UNSPECIFIED FORM; LACTOSE, UNSPECIFIED FORM; SUCROSE; LACTOSE, UNSPECIFIED FORM; SUCROSE; SUCROSE; LACTOSE, UNSPECIFIED FORM; SUCROSE; LACTOSE, UNSPECIFIED FORM; SUCROSE; LACTOSE, UNSPECIFIED FORM; SUCROSE; LACTOSE, UNSPECIFIED FORM; LACTOSE, UNSPECIFIED FORM; SUCROSE; LACTOSE, UNSPECIFIED FORM; SUCROSE; SUCROSE; LACTOSE, UNSPECIFIED FORM; SUCROSE; LACTOSE, UNSPECIFIED FORM; SUCROSE; LACTOSE, UNSPECIFIED FORM; LACTOSE, UNSPECIFIED FORM; SUCROSE; LACTOSE, UNSPECIFIED FORM; SUCROSE; SUCROSE; LACTOSE, UNSPECIFIED FORM; SUCROSE; LACTOSE, UNSPECIFIED FORM; SUCROSE; LACTOSE, UNSPECIFIED FORM; LACTOSE, UNSPECIFIED FORM; SUCROSE; LACTOSE, UNSPECIFIED FORM; SUCROSE; SUCROSE; LACTOSE, UNSPECIFIED FORM; SUCROSE; LACTOSE, UNSPECIFIED FORM; LACTOSE, UNSPECIFIED FORM; SUCROSE; SUCROSE; LACTOSE, UNSPECIFIED FORM; LACTOSE, UNSPECIFIED FORM; SUCROSE; SUCROSE; LACTOSE, UNSPECIFIED FORM; SUCROSE; LACTOSE, UNSPECIFIED FORM; LACTOSE, UNSPECIFIED FORM; SUCROSE; SUCROSE; LACTOSE, UNSPECIFIED FORM; SUCROSE; LACTOSE, UNSPECIFIED FORM; LACTOSE, UNSPECIFIED FORM; SUCROSE; SUCROSE; LACTOSE, UNSPECIFIED FORM; SUCROSE; LACTOSE, UNSPECIFIED FORM; SUCROSE; LACTOSE, UNSPECIFIED FORM; LACTOSE, UNSPECIFIED FORM; SUCROSE; SUCROSE; LACTOSE, UNSPECIFIED FORM; SUCROSE; LACTOSE, UNSPECIFIED FORM; SUCROSE; LACTOSE, UNSPECIFIED FORM; LACTOSE, UNSPECIFIED FORM; SUCROSE; SUCROSE; LACTOSE, UNSPECIFIED FORM; LACTOSE, UNSPECIFIED FORM; SUCROSE; SUCROSE; LACTOSE, UNSPECIFIED FORM; SUCROSE; LACTOSE, UNSPECIFIED FORM; LACTOSE, UNSPECIFIED FORM; SUCROSE; LACTOSE, UNSPECIFIED FORM; SUCROSE; SUCROSE; LACTOSE, UNSPECIFIED FORM; LACTOSE, UNSPECIFIED FORM; SUCROSE; LACTOSE, UNSPECIFIED FORM; SUCROSE; SUCROSE; LACTOSE, UNSPECIFIED FORM; LACTOSE, UNSPECIFIED FORM; SUCROSE

Complete 30C/200C Homeopathic Kit

ACTIVE INGREDIENTS

Acon nap 30c
Aesculus hipp 30c
Allium cepa 30c
Antimon crud 30c
Apis mel 30c
Arnica 30c
Arsenicum alb 30c
Belladonna 30c
Bellis 30c
Berber vulg 30c
Bryonia 30c
Calc carb 30c
Caulophyllum 30c
Causticum 30c
Chamomilla 30c
Cimicifuga 30c
Coffea cruda 30c
Drosera 30c
Eupatorium perf 30c
Euphrasia 30c
Ferrum phos 30c
Gelsemium 30c
Hamamelis 30c
Hepar sulph calc 30c
Hydrastis 30c
Hypericum 30c
Ignatia 30c
Ipecac 30c
Kali bic 30c
Kali carb 30c
Kali mur 30c
Kali phos 30c
Lachesis 30c
Ledum 30c
Lycopodium 30c
Mag phos 30c
Nat mur 30c
Nux vom 30c
Petroleum 30c
Phosphoricum ac 30c
Phytolacca 30c
Podoph pelt 30c
Pulsatilla 30c
Rhus tox 30c
Ruta 30c
Sepia 30c
Staphysag 30c
Sulphur 30c
Symphytum 30c
Thuja occ 30c

Acon nap 200c
Aesculus hipp 200c
Allium cepa 200c
Antimon crud 200c
Apis mel 200c
Arnica 200c
Arsenicum alb 200c
Belladonna 200c
Bellis 200c
Berber vulg 200c
Bryonia 200c
Calc carb 200c
Caulophyllum 200c
Causticum 200c
Chamomilla 200c
Cimicifuga 200c
Coffea cruda 200c
Drosera 200c
Eupatorium perf 200c
Euphrasia 200c
Ferrum phos 200c
Gelsemium 200c
Hamamelis 200c
Hepar sulph calc 200c
Hydrastis 200c
Hypericum 200c
Ignatia 200c
Ipecac 200c
Kali bic 200c
Kali carb 200c
Kali mur 200c
Kali phos 200c
Lachesis 200c
Ledum 200c
Lycopodium 200c
Mag phos 200c
Nat mur 200c
Nux vom 200c
Petroleum 200c
Phosphoricum ac 200c
Phytolacca 200c
Podoph pelt 200c
Pulsatilla 200c
Rhus tox 200c
Ruta 200c
Sepia 200c
Staphysag 200c
Sulphur 200c
Symphytum 200c
Thuja occ 200c

USES

To relieve symptoms of fear, hemorrhoids, head cold, warts, stings, bruises, vomiting, fever, bruised soreness, itching, worse motion, oberwork, cramps, hoarseness, irritability, minor back pain, sleeplessness, cough, flu-like symptoms, eye irritation, low fever, lethargy, varicose veins, croupiness, sinuses, shooting pain, sadness, nausea, sinuses, sour belching, congested ears, irritability, sore throat, black eyes, digestion, cramps, sneezing, vomiting, nausea, headache, sore throat, diarrhea, weeping, better motion, bruised feeling, indifference, anger, skin problems, prickling pain, and warts.

KEEP OUT OF REACH OF CHILDREN

Keep this and all medicines out of reach of children.

INDICATIONS

Acon nap fear

Aesculus hipp hemorrhoids

Allium cepa head cold

Antimon crud warts

Apis mel stings

Arnica bruises

Arsenicum alb vomiting

Belladonna fever

Bellis bruised soreness

Berber vulg itching

Bryonia worse motion

Calc carb overwork

Caulophyllum cramps

Causticum hoarseness

Chamomilla irritability

Cimicifuga minor back pain

Coffea cruda sleeplessness

Drosera cough

Eupatorium perf flu-like symptoms

Euphrasia eye irritation

Ferrum phos low fever

Gelsemium lethargy

Hamamelis varicose veins

Hepar sulph calc croupiness

Hydrastis sinuses

Hypericum shooting pain

Ignatia sadness

Ipecac nausea

Kali bic sinuses

Kali carb sour belching

Kali mur congested ears

Kali phos irritability

Lachesis sore throat

Ledum black eyes

Lycopodium digestion

Mag phos cramps

Nat mur sneezing

Nux vom vomiting

Petroleum nausea

Phosphoricum ac headache

Phytolacca sore throat

Podoph pelt diarrhea

Pulsatilla weeping

Rhus tox better motion

Ruta bruised feeling

Sepia indifference

Staphysag anger

Sulphur skin problems

Symphytum prickling pain

Thuja occ warts

STOP USE AND ASK DOCTOR

If symptoms persist/worsen or if pregnant/nursing, stop use and consult your practitioner.

DIRECTIONS

Adults: Dissolve 3 to 5 under the tongue three times a day or as directed by a licensed practitioner. Take at greater intervals as condition subsides.

Children: Dissolve 3 to 5 under the tongue three times a day or as directed by a licensed practitioner. Take at greater intervals as condition subsides.

INACTIVE INGREDIENTS

Sucrose/Lactose